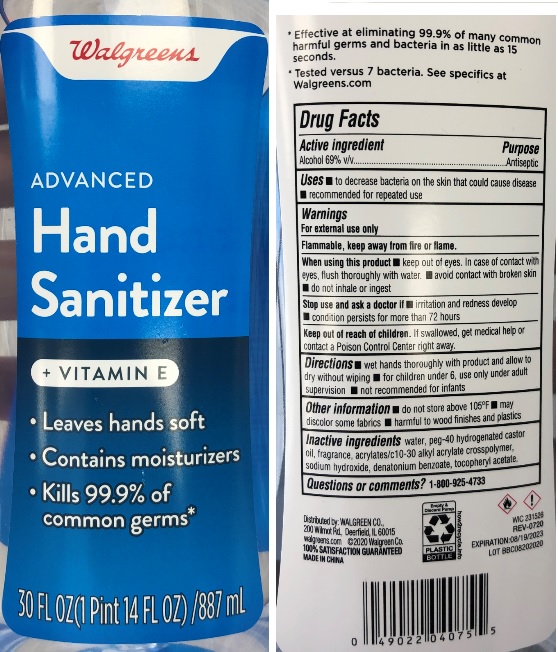 DRUG LABEL: Walgreens Advanced Hand Sanitizer with Vitamin E
NDC: 0363-9008 | Form: GEL
Manufacturer: Walgreen Company
Category: otc | Type: HUMAN OTC DRUG LABEL
Date: 20201208

ACTIVE INGREDIENTS: ALCOHOL 69 mL/100 mL
INACTIVE INGREDIENTS: DENATONIUM BENZOATE; POLYOXYL 40 HYDROGENATED CASTOR OIL; CARBOMER COPOLYMER TYPE A (ALLYL PENTAERYTHRITOL CROSSLINKED); .ALPHA.-TOCOPHEROL ACETATE; WATER; SODIUM HYDROXIDE

Walgreens Advanced Hand Sanitizer with Vitamin E

Active ingredient

Alcohol 69% v/v

Purpose

Antiseptic

Uses

- to decrease bacteria on the skin that could cause disease
- recommended for repeated use

Warnings

For external use only

Flammable, keep away from fire or flame.

When using this product

- keep out of eyes. In case of contact with eyes, flush thoroughly with water.
- avoid contact with broken skin
- do not inhale or ingest

Stop use and ask a doctor if

- irritation and redness develop
- condition persists for more than 72 hours

Keep out of reach of children.

If swallowed, get medical help or contact a Poison Control Center right away.

Directions

- wet hands thoroughly with product and allow to dry without wiping
- for children under 6, use only under adult supervision
- not recommended for infants

Other information

- do not store above 105F
- may discolor some fabric
- harmful to wood finishes and plastics

Inactive ingredients

water, peg-40 hydrogenated castor oil, fragrance, acrylates/c10-30 alkyl acrylate crosspolymer, sodium hydroxide, denatonium benzoate, tocopheryl acetate.

Questions or comments?

1-800-925-4733

Company Information

Distributed by: Walgreen Co.

200 Wilmot Rd, Deerfield, IL 60015

walgreens.com